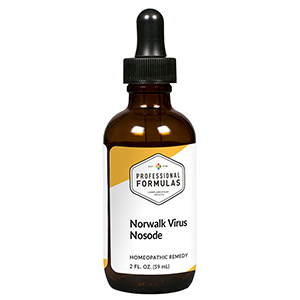 DRUG LABEL: Norwalk Virus Nosode
NDC: 63083-4035 | Form: LIQUID
Manufacturer: Professional Complementary Health Formulas
Category: homeopathic | Type: HUMAN OTC DRUG LABEL
Date: 20190815

ACTIVE INGREDIENTS: NORWALK VIRUS 30 [hp_X]/59 mL
INACTIVE INGREDIENTS: ALCOHOL; WATER

N35

ACTIVE INGREDIENTS

Norovirus (Norwalk virus) 30X, 60X

QUESTIONS

Professional Formulas

PO Box 2034 Lake Oswego, OR 97035

INDICATIONS

For the temporary relief of nausea or vomiting, abdominal pain or cramps, diarrhea, muscle pain, or feelings of discomfort or uneasiness.*

PURPOSE

*Claims based on traditional homeopathic practice, not accepted medical evidence. Not FDA evaluated.

WARNINGS

Consult a doctor if condition worsens or if symptoms persist. Keep out of the reach of children. In case of overdose, get medical help or contact a poison control center right away. If pregnant or breastfeeding, ask a healthcare professional before use.

Keep out of the reach of children.

PREGNANCY OR BREAST FEEDING

If pregnant or breastfeeding, ask a healthcare professional before use.

DIRECTIONS

Place drops under tongue 30 minutes before/after meals. Adults and children 12 years and over: Take 10 to 15 drops once weekly or monthly. If mild symptoms are present, take 10 drops up to 3 times per day. Consult a physician for use in children under 12 years of age.

OTHER INFORMATION

Tamper resistant. If seal is broken, do not use. After opening, close container tightly and store at room temperature away from heat.

INACTIVE INGREDIENTS

20% ethanol, purified water.

LABEL

Est 1985

Professional Formulas

Complementary Health

Norwalk Virus Nosode

Homeopathic Remedy

2 FL. OZ. (59 mL)